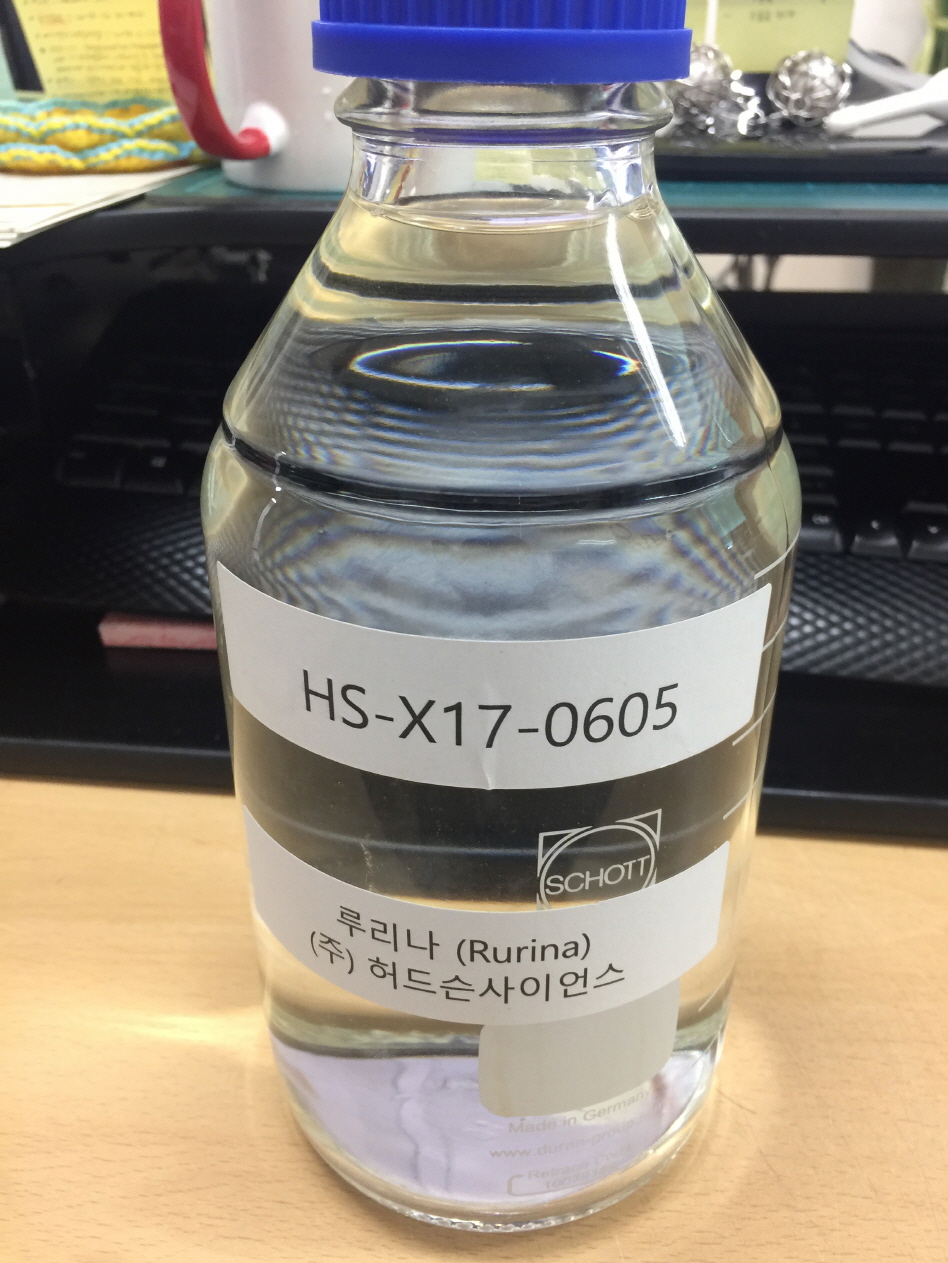 DRUG LABEL: Rurina
NDC: 71608-0001 | Form: LIQUID
Manufacturer: NANO BIO TECH CO.,Ltd
Category: otc | Type: HUMAN OTC DRUG LABEL
Date: 20180101

ACTIVE INGREDIENTS: SULFATE ION 3.6 g/1 L; POTASSIUM CATION 0.25 g/1 L; CHLORIDE ION 0.11 g/1 L
INACTIVE INGREDIENTS: MAGNESIUM

ACTIVE INGREDIENT

Sulfate, Potassium Ion, Chloride Ion

INACTIVE INGREDIENT

Al, Ca, Ga, La, Li, Mn, Nd, Si, Zn

PURPOSE

First aid to help prevent infection in minor:

- cuts
- scrapes
- burns

Do not use

- if you are allergic to any of the ingredients
- in the eyes
- over large areas of the body

Ask a doctor before use if you have

- deep or puncture wounds
- animal bites
- serious burns

Stop use and ask a doctor if

- you need to use longer than 1 week
- condition persists or gets worse
- rash or other allergic reaction develops

Keep out of reach of children.

INDICATIONS AND USAGE

Apply to the area which is wounded or burnt

DOSAGE AND ADMINISTRATION

for external use only